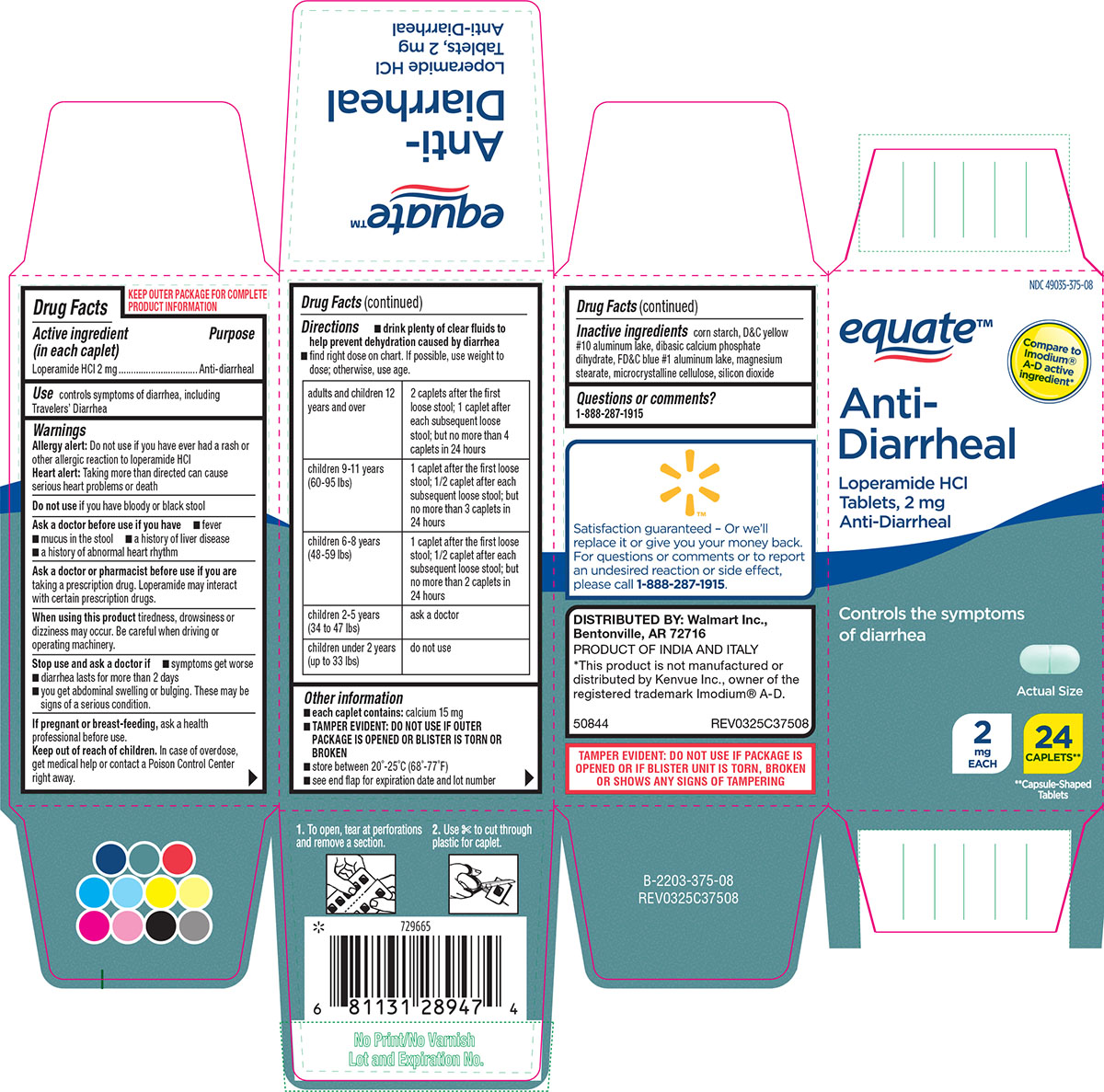 DRUG LABEL: Anti Diarrheal
NDC: 49035-375 | Form: TABLET
Manufacturer: Wal-Mart Stores Inc
Category: otc | Type: HUMAN OTC DRUG LABEL
Date: 20260119

ACTIVE INGREDIENTS: LOPERAMIDE HYDROCHLORIDE 2 mg/1 1
INACTIVE INGREDIENTS: STARCH, CORN; D&C YELLOW NO. 10 ALUMINUM LAKE; DIBASIC CALCIUM PHOSPHATE DIHYDRATE; FD&C BLUE NO. 1 ALUMINUM LAKE; MAGNESIUM STEARATE; MICROCRYSTALLINE CELLULOSE; SILICON DIOXIDE

Equate 44-375

Active ingredient (in each caplet)

Loperamide HCl 2 mg

Purpose

Anti-diarrheal

Use

controls symptoms of diarrhea, including Travelers’ Diarrhea

Warnings

Allergy alert: Do not use if you have ever had a rash or other allergic reaction to loperamide HCl
Heart alert: Taking more than directed can cause serious heart problems or death

Do not use

if you have bloody or black stool

Ask a doctor before use if you have

- fever
- mucus in the stool
- a history of liver disease
- a history of abnormal heart rhythm

Ask a doctor or pharmacist before use if you are

taking a prescription drug. Loperamide may interact with certain prescription drugs.

When using this product

tiredness, drowsiness or dizziness may occur. Be careful when driving or operating machinery.

Stop use and ask a doctor if

- symptoms get worse
- diarrhea lasts for more than 2 days
- you get abdominal swelling or bulging. These may be signs of a serious condition.

If pregnant or breast-feeding,

ask a health professional before use.

Keep out of reach of children.

In case of overdose, get medical help or contact a Poison Control Center right away.

Directions

- drink plenty of clear fluids to help prevent dehydration caused by diarrhea
- find right dose on chart. If possible, use weight to dose; otherwise, use age.

adults and children 12 years and over | 2 caplets after the first loose stool; 1 caplet after each subsequent loose stool; but no more than 4 caplets in 24 hours
children 9-11 years (60-95 lbs) | 1 caplet after the first loose stool; 1/2 caplet after each subsequent loose stool; but no more than 3 caplets in 24 hours
children 6-8 years (48-59 lbs) | 1 caplet after the first loose stool; 1/2 caplet after each subsequent loose stool; but no more than 2 caplets in 24 hours
children 2-5 years (34 to 47 lbs) | ask a doctor
children under 2 years (up to 33 lbs) | do not use

Other information

- each caplet contains: calcium 15 mg
- TAMPER EVIDENT: DO NOT USE IF OUTER PACKAGE IS OPENED OR BLISTER IS TORN OR BROKEN
- store between 20°-25°C (68°-77°F)
- see end flap for expiration date and lot number

Inactive ingredients

corn starch, D&C yellow #10 aluminum lake, dibasic calcium phosphate dihydrate, FD&C blue #1 aluminum lake, magnesium stearate, microcrystalline cellulose, silicon dioxide

Questions or comments?

1-888-287-1915

Principal Display Panel

NDC 49035-375-08

equate™

Compare to
Imodium®
A-D active
ingredient*

Anti-
Diarrheal
Loperamide HCl
Tablets, 2 mg
Anti-Diarrheal

Controls the symptoms
of diarrhea

Actual Size

2
mg
EACH

24
CAPLETS**
**Capsule-Shaped
Tablets

Satisfaction guaranteed - Or we'll
replace it or give you your money back.
For questions or comments or to report
an undesired reaction or side effect,
please call 1-888-287-1915.

DISTRIBUTED BY: Walmart Inc.,
Bentonville, AR 72716

PRODUCT OF INDIA AND ITALY

*This product is not manufactured or
distributed by Kenvue Inc., owner of the
registered trademark Imodium® A-D.

50844 REV0325C37508

TAMPER EVIDENT: DO NOT USE IF PACKAGE IS
OPENED OR IF BLISTER UNIT IS TORN, BROKEN
OR SHOWS ANY SIGNS OF TAMPERING

1. To open, tear at perforations
and remove a section.

2. Use ✄ to cut through
plastic for caplet.

Equate 44-375